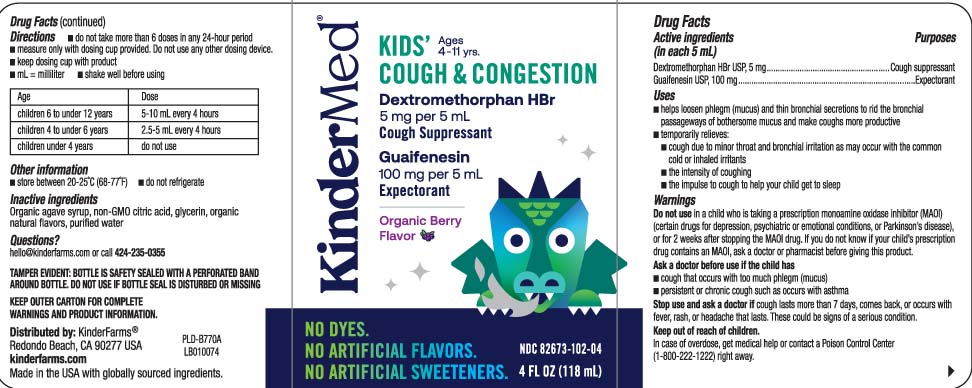 DRUG LABEL: Mucus Relief Cough and Congestion
NDC: 82673-102 | Form: LIQUID
Manufacturer: KinderFarms, LLC
Category: otc | Type: HUMAN OTC DRUG LABEL
Date: 20241004

ACTIVE INGREDIENTS: DEXTROMETHORPHAN HYDROBROMIDE 5 mg/5 mL; GUAIFENESIN 100 mg/5 mL
INACTIVE INGREDIENTS: AGAVE TEQUILANA JUICE; CITRIC ACID MONOHYDRATE; GLYCERIN; WATER

Drug Facts

Active ingredients (in each 5 mL)

Dextromethorphan HBr USP, 5 mg

Guaifenesin USP, 100 mg

Purposes

Cough suppressant

Expectorant

Uses

- helps loosen phlegm (mucus) and thin bronchial secretions to rid the bronchial passageways of bothersome mucus and make coughs more productive
- temporarily relieves:
  - cough due to minor throat and bronchial irritation as may occur with the common cold or inhaled irritants
  - the intensity of coughing
  - the impulse to cough to help your child get to sleep

Warnings

Do not use

in a child who is taking a prescription monoamine oxidase inhibitor (MAOI) (certain drugs for depression, psychiatric or emotional conditions, or Parkinson's disease), or for 2 weeks after stopping the MAOI drug. If you do not know if your child's prescription drug contains an MAOI, ask a doctor or pharmacist before taking this product.

Ask a doctor before use if the child has

- cough that occurs with too much phlegm (mucus)
- persistent or chronic cough such as occurs with asthma

Stop use and ask a doctor if

cough lasts more than 7 days, comes back, or occurs with fever, rash, or headache that lasts. These could be signs of a serious condition.

Keep out of reach of children.

In case of overdose, get medical help or contact a Poison Control Center (1-800-222-1222) right away.

Directions

- do not take more than 6 doses in any 24-hour period
- measure only with dosing cup provided. Do not use any other dosing device.
- keep dosing cup with product
- mL = milliliter
- shake well before using

age | dose
children 6 to under 12 years | 5-10 mL every 4 hours
children 4 to under 6 years | 2.5-5 mL every 4 hours
children under 4 years | do not use

Other information

- store between 20-25ºC (68-77ºF).
- do not refrigerate.

Inactive ingredients

Organic agave syrup, non-GMO citric acid, glycerin, organic natural flavor, purified water

QUESTION?

Call 424-235-0355

Principal Display Panel

KIDS' COUGH & CONGESTION Ages 4-11 yrs

Dextromethorphan HBr

5 mg per 5 mL

Cough Suppressant

Guaifenesin

100 mg per 5 mL

Expectorant

Organic Berry Flavor

NO DYES.

NO ARTIFICIAL FLAVORS.

NO ARTIFICIAL SWEETENERS.

DOSAGE CUP PROVIDED

FL OZ (mL)

TAMPER EVIDENT: BOTTLE IS SAFETY SEALED WITH A PERFORATED BAND AROUND BOTTLE. DO NOT USE IF BOTTLE SEAL IS DISTURBED OR MISSING.

KEEP OUTER CARTON FOR COMPLETE WARNINGS AND PRODUCT INFORMATION

DISTRIBUTED BY: KinderFarms®

Redondo Beach, CA 90277

kinderfarms.com

Package Label

KINDERMED Kids Cough and Congestion Organic Berry Flavor